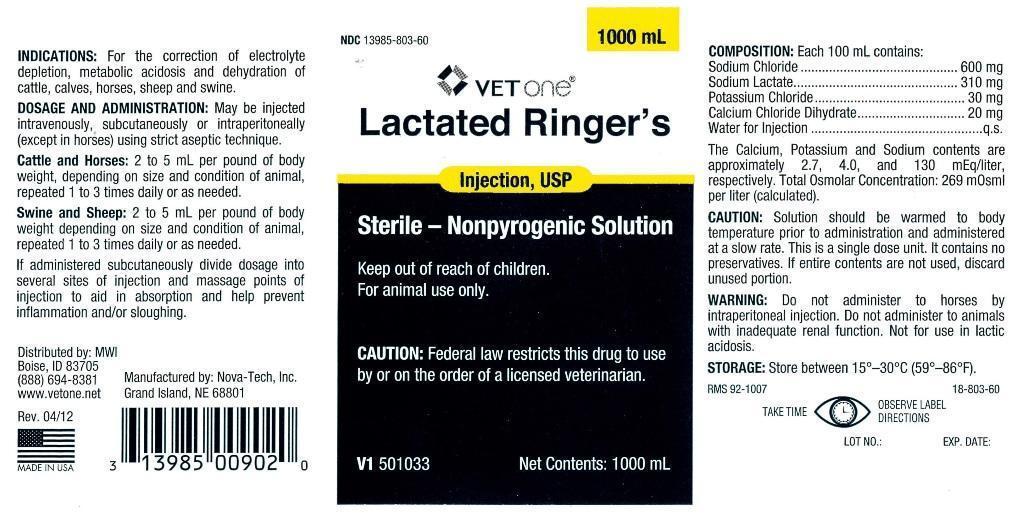 DRUG LABEL: Lactated Ringers
NDC: 13985-803 | Form: INJECTION, SOLUTION
Manufacturer: MWI (VetOne)
Category: animal | Type: PRESCRIPTION ANIMAL DRUG LABEL
Date: 20240425

ACTIVE INGREDIENTS: SODIUM CHLORIDE 600 mg/100 mL; SODIUM LACTATE 310 mg/100 mL; POTASSIUM CHLORIDE 30 mg/100 mL; CALCIUM CHLORIDE 20 mg/100 mL

Lactated Ringers

INDICATIONS:

For the correction of electrolyte depletion, metabolic acidosis and dehydration of cattle, calves, horses, sheep and swine.

DOSAGE AND ADMINISTRATION:

May be injected intravenously, subcutaneously or intraperitoneally (except in horses) using strict aseptic technique.

Cattle and Horses: 2 to 5 mL per pound of body weight, depending on size and condition of animal, repeated 1 to 3 times daily or as needed.

Swine and Sheep: 2 to 5 mL per pound of body weight depending on size and condition of animal, repeated 1 to 3 times daily or as needed.

If administered subcutaneously divide dosage into several sites of injection and massage points of injection to aid in absorption and help prevent inflammation and/or sloughing.

INFORMATION FOR OWNERS/CAREGIVERS

Distributed by: MWI
Boise, ID 83705
(888) 694-8381
www.vetone.net

Manufactured by: Nova-Tech, Inc.
Grand Island, NE 68801

Rev. 04/12

V1 501033

Net Contents: 1000 mL

RMS 92-1007

18-803-60

LOT NO.: EXP. DATE:

NDC 13985-803-60

1000 mL

MADE IN USA

VETERINARY INDICATIONS

Sterile - Nonpyrogenic Solution

For animal use only.

Keep out of reach of children.

CAUTION:

Federal law restricts this drug to use by or on the order of a licensed veterinarian.

COMPOSITION:

Each 100 mL contains:
Sodium Chloride........................600 mg
Sodium Lactate.........................310 mg
Potassium Chloride.....................30 mg
Calcium Chloride Dihydrate..........20 mg
Water for Injection.........................q.s.

The Calcium, Potassium and Sodium contents are approximately 2.7, 4.0, and 130 mEq/liter, respectively. Total Osmolar Concentration: 269 mOsml per liter (calculated).

CAUTION:

Solution should be warmed to body temperature prior to administration and administered at a slow rate. This is a single dose unit. It contains no preservatives. If entire contents are not used, discard unused portion.

WARNING:

Do not administer to horses by intraperitoneal injection. Do not administer to animals with inadequate renal function. Not for use in lactic acidosis.

STORAGE:

Store between 15° - 30°C (59° - 86°F).

PRECAUTIONS

TAKE TIME OBSERVE LABEL DIRECTIONS